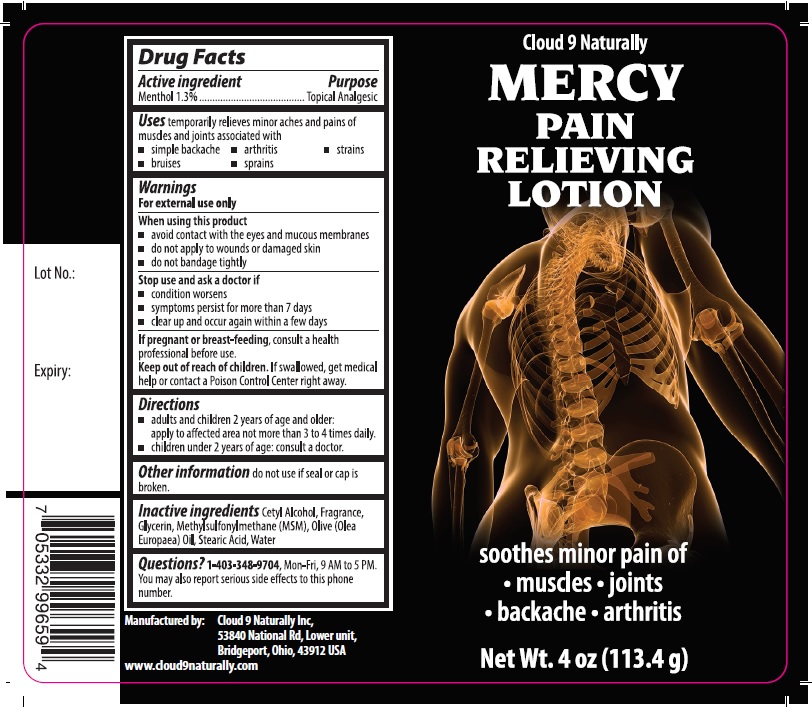 DRUG LABEL: MERCY PAIN RELIEVING
NDC: 72070-100 | Form: LOTION
Manufacturer: Cloud 9 Naturally
Category: otc | Type: HUMAN OTC DRUG LABEL
Date: 20180518

ACTIVE INGREDIENTS: MENTHOL, UNSPECIFIED FORM 1.3 g/100 g
INACTIVE INGREDIENTS: CETYL ALCOHOL; GLYCERIN; DIMETHYL SULFONE; OLIVE OIL; STEARIC ACID; WATER

MERCY PAIN RELIEVING LOTION

Active ingredient

Menthol 1.3%

Purpose

Topical Analgesic

Uses

temporarily relieves minor aches and pains of muscles and joints associated with

• simple backache • arthritis • strains • bruises • sprains

Warnings

For external use only

When using this product

• avoid contact with the eyes and mucous membranes

• do not apply to wounds or damaged skin

• do not bandage tightly

Stop use and ask a doctor if

• condition worsens

• symptoms persist for more than 7 days

• clear up and occur again within a few days

If pregnant or breast-feeding, consult a health professional before use.

Keep out of reach of children. If swallowed, get medical help or contact a Poison Control Center right away.

Directions

• adults and children 2 years of age and older: apply to affected area not more than 3 to 4 times daily.

• children under 2 years of age: consult a doctor.

Inactive ingredients

Cetyl Alcohol, Fragrance, Glycerin, Methylsulfonylmethane (MSM), Olive (Oleo Europaea) Oil, Stearic Acid, Water

Other information

do not use if seal or cap is broken.

Questions?

1-403-348-9704, Mon-Fri, 9AM to 5 PM.

You may also report serious side effects to this phone number.

Soothes minor pain of

• muscles • joints • backache • arthritis

Manufactured by:

Cloud 9 Naturally Inc,

53840 National Rd, Lower unit,

Bridgeport, Ohio, 43912 USA

www.cloud9naturally.com